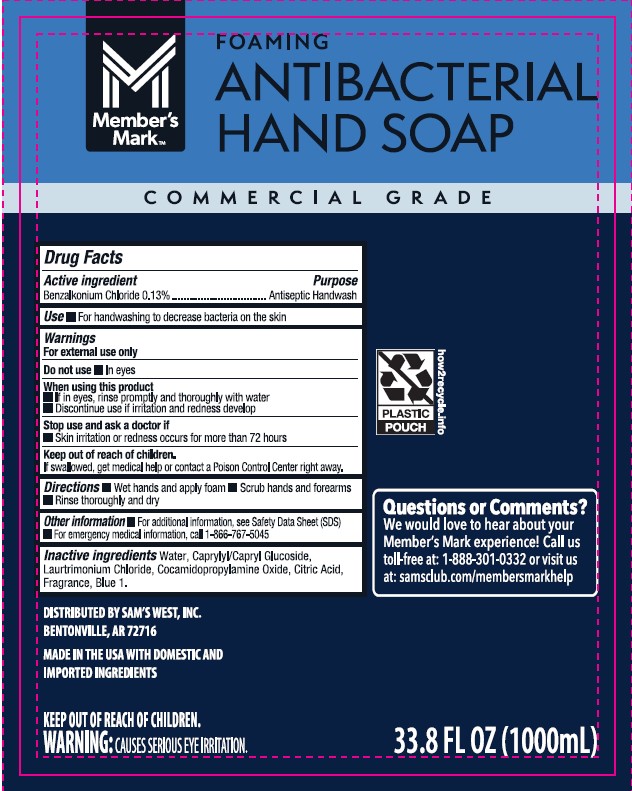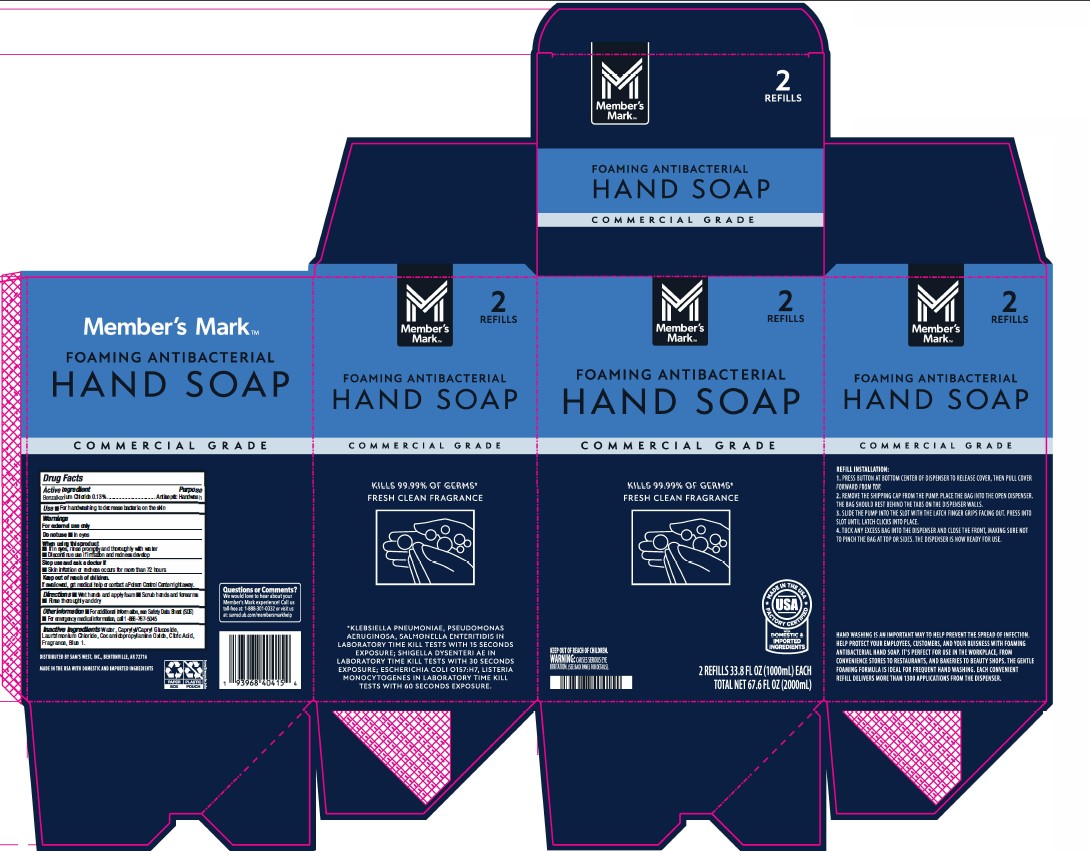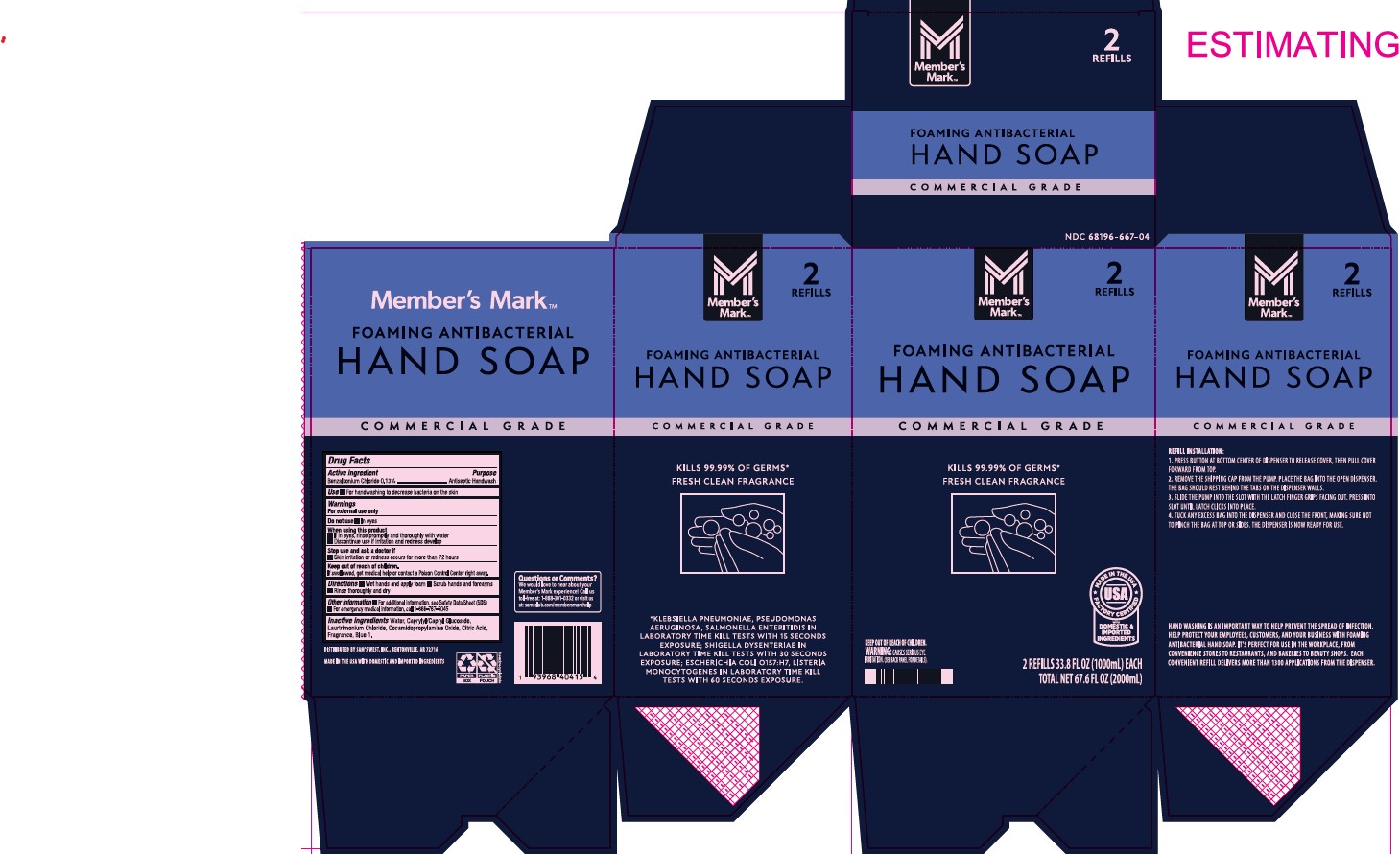 DRUG LABEL: Foaming Antibacterial
NDC: 68196-667 | Form: SOLUTION
Manufacturer: Sam's West, Inc.
Category: otc | Type: HUMAN OTC DRUG LABEL
Date: 20250124

ACTIVE INGREDIENTS: BENZALKONIUM CHLORIDE 1.3 g/1000 mL
INACTIVE INGREDIENTS: COCAMIDOPROPYLAMINE OXIDE; ANHYDROUS CITRIC ACID; FD&C BLUE NO. 1; CAPRYLYL/CAPRYL OLIGOGLUCOSIDE; WATER; LAURTRIMONIUM CHLORIDE

Foaming Antibacterial 68196-667

Active Ingredient

Benzalkonium Chloride 0.13%

Purpose

Antiseptic Handwash

Use

- For handwashing to decrease bacteria on the skin

Warnings

For external use only

Do not use

- In eyes

When using this product

- If in eyes, rinse promptly and thoroughly with water
- Discontinue use if irritation and redness develop

Stop use and ask a doctor if

- Skin irritation or redness occurs for more than 72 hours

Keep out of reach of children.

If swallowed, get medical help or contact a Poison Control Center right away.

Directions

- Wet hands and apply foam
- Scrub hands and forearms
- Rinse thoroughly and dry

Other information

- For additional information, see Safety Data Sheet (SDS)
- For emergency medical information, call 1-866-767-5045

INACTIVE INGREDIENT

Inactive ingredientsWater, Caprylyl/Capryl Glucoside, Laurtrimonium Chloride, Cocamidopropylamine Oxide, Citric Acid, Fragrance, Blue 1.

PACKAGE LABEL

Member's Mark

2 REFILLS

FOAMING ANTIBACTERIAL

HAND SOAP

COMMERCIAL GRADE

KILLS 99.99% OF GERMS*

FRESH CLEAN FRAGRANCE

KEEP OUT OF REACH OF CHILDREN.

WARNING: CAUSES SERIOUS EYE

IRRITATION (SEE BACK PANEL FOR DETAILS).

2 REFILLS 33.8 FL OZ (1000mL) EACH

TOTAL NET 67.6 FL OZ (2000mL)